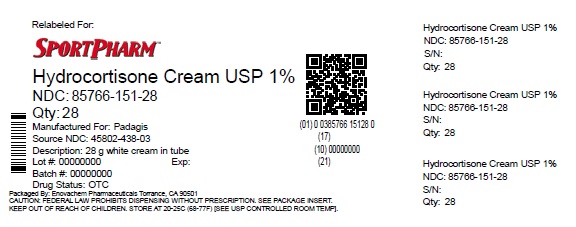 DRUG LABEL: hydrocortisone
NDC: 85766-151 | Form: CREAM
Manufacturer: Sportpharm LLC
Category: otc | Type: HUMAN OTC DRUG LABEL
Date: 20260206

ACTIVE INGREDIENTS: HYDROCORTISONE 1 g/100 g
INACTIVE INGREDIENTS: WATER; CETOSTEARYL ALCOHOL; POLYOXYL 20 CETOSTEARYL ETHER; DIAZOLIDINYL UREA; SORBIC ACID; CETYL PALMITATE; GLYCERIN; ISOPROPYL MYRISTATE; ISOSTEARYL NEOPENTANOATE; ALOE VERA LEAF; BUTYLATED HYDROXYTOLUENE; SODIUM HYDROXIDE

Hydrocortisone Cream 1%Drug Facts

Active ingredient

Hydrocortisone 1%

Purpose

Anti-itch

Uses

- temporarily relieves itching associated with minor skin irritations, inflammation, and rashes due to:
- eczema
- insect bites
- poison ivy, oak, or sumac
- soaps
- detergents
- cosmetics
- jewelry
- seborrheic dermatitis
- psoriasis
- temporarily relieves external anal and genital itching
- other uses of this product should only be under the advice and supervision of a doctor

Warnings

For external use only

Do not use

- in the genital area if you have a vaginal discharge. Consult a doctor.
- for the treatment of diaper rash. Consult a doctor.

When using this product

- avoid contact with eyes
- do not use more than directed unless told to do so by a doctor
- do not put directly into the rectum by using fingers or any mechanical device or applicator

Stop use and ask a doctor if

- rectal bleeding occurs
- condition worsens, symptoms persist for more than 7 days or clear up and occur again within a few days, and do not use this or any other hydrocortisone product unless you have asked a doctor

Keep out of reach of children.

If swallowed, get medical help or contact a Poison Control Center right away (1-800-222-1222).

Directions

- for itching of skin irritation, inflammation, and rashes:
- adults and children 2 years of age and older: apply to affected area not more than 3 to 4 times daily
- children under 2 years of age: ask a doctor
- for external anal and genital itching, adults:
- when practical, cleanse the affected area with mild soap and warm water and rinse thoroughly
- gently dry by patting or blotting with toilet tissue or a soft cloth before applying
- apply to affected area not more than 3 to 4 times daily
- children under 12 years of age: ask a doctor

Other information

- store at 20-25°C (68-77°F)

Inactive ingredients

water, cetearyl alcohol, cetyl palmitate, glycerin, isopropyl myristate, isostearyl neopentanoate, ceteareth-20, diazolidinyl urea, sorbic acid, aloe barbadensis leaf juice, BHT, sodium hydroxide

Questions or comments?

1-800-719-9260